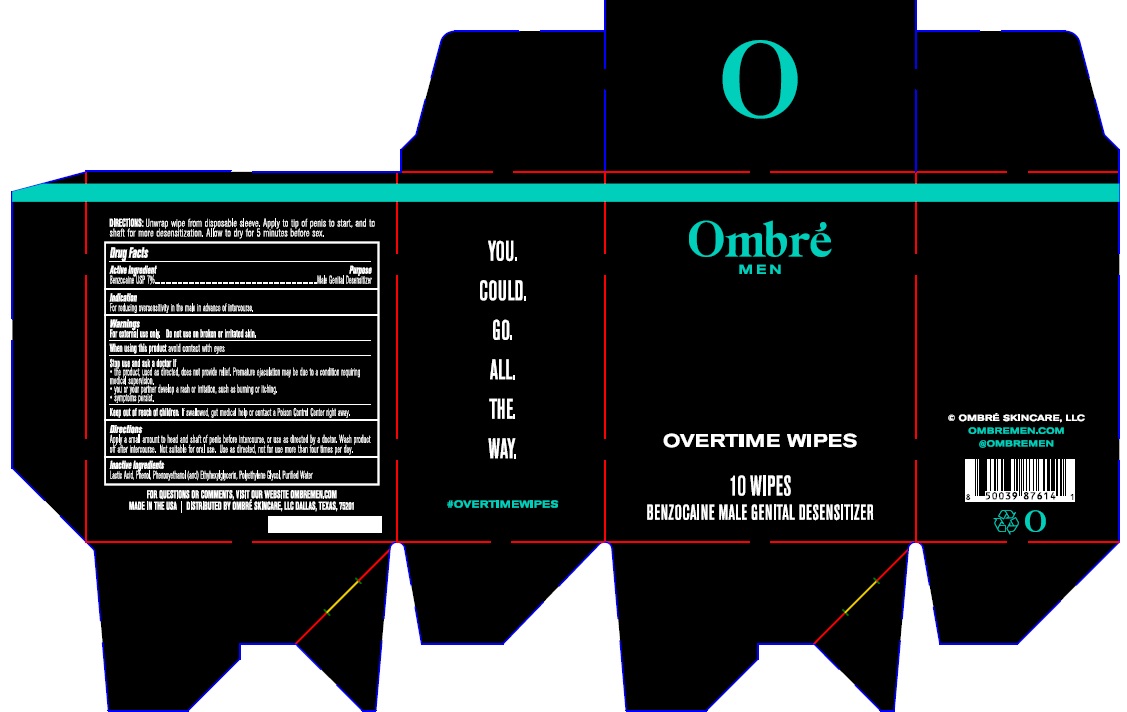 DRUG LABEL: Ombre Men overtime wipes
NDC: 54723-007 | Form: CLOTH
Manufacturer: Sambria Pharmaceuticals, LLC
Category: otc | Type: HUMAN OTC DRUG LABEL
Date: 20251007

ACTIVE INGREDIENTS: BENZOCAINE 7 g/100 mL
INACTIVE INGREDIENTS: WATER; LACTIC ACID, UNSPECIFIED FORM; PHENOL; PHENOXYETHANOL; ETHYLHEXYLGLYCERIN; POLYETHYLENE GLYCOL, UNSPECIFIED

Active ingredient

Benzocaine USP 7%

Purpose

Male Genital Desensitizer

Indication

For reducing oversensitivity in the male in advance of intercourse,

Warnings

For External Use only. Do not use onbroken or irritated skin.
When using this avoid contact with eyes.
Stop and ask doctor if:

- the product, used as directed, does not provide relief. Premature ejaculation may be due to a condition requiring medical supervision.
- you or your partner develop rash or irritation, such as burning or itching.
- symptoms persist.

Keep out of reach of children

If swallowed, get medical help or contact a Poison Control Center right away.

Directions

Apply a small amount to head and shaft of penis before intercourse, or use as directed by a doctor. Wash product off after intercourse. Not suitable for oral use. Use as directed, not for use more than four times per day.

For Questions or Comments, visit our website OMBREMEN.COM

Inactive ingredients

Lactic Acid, Phenol, Phenoxyethanol, Ethylhexylglycerin, Polyethylene Glycol, purified water